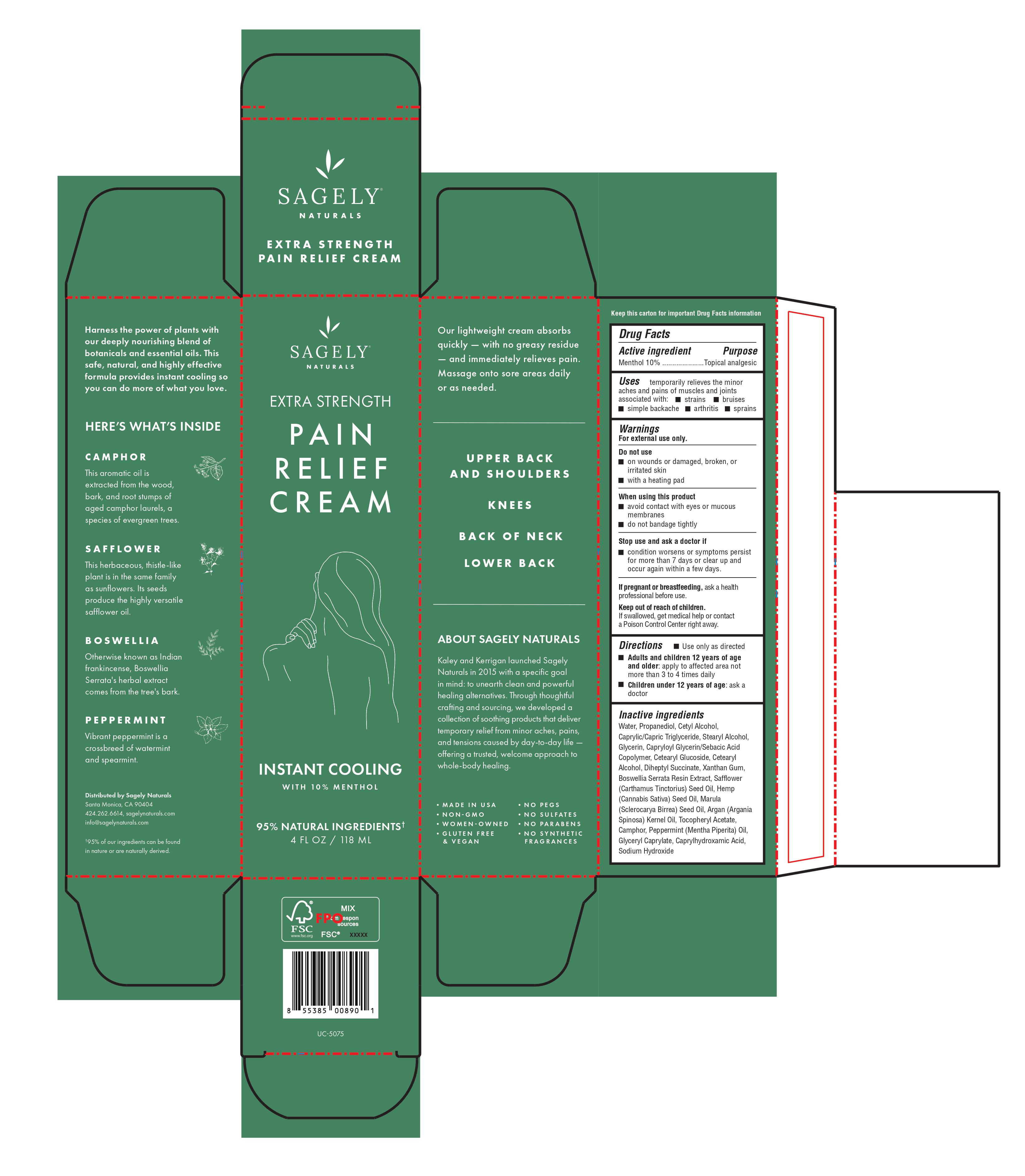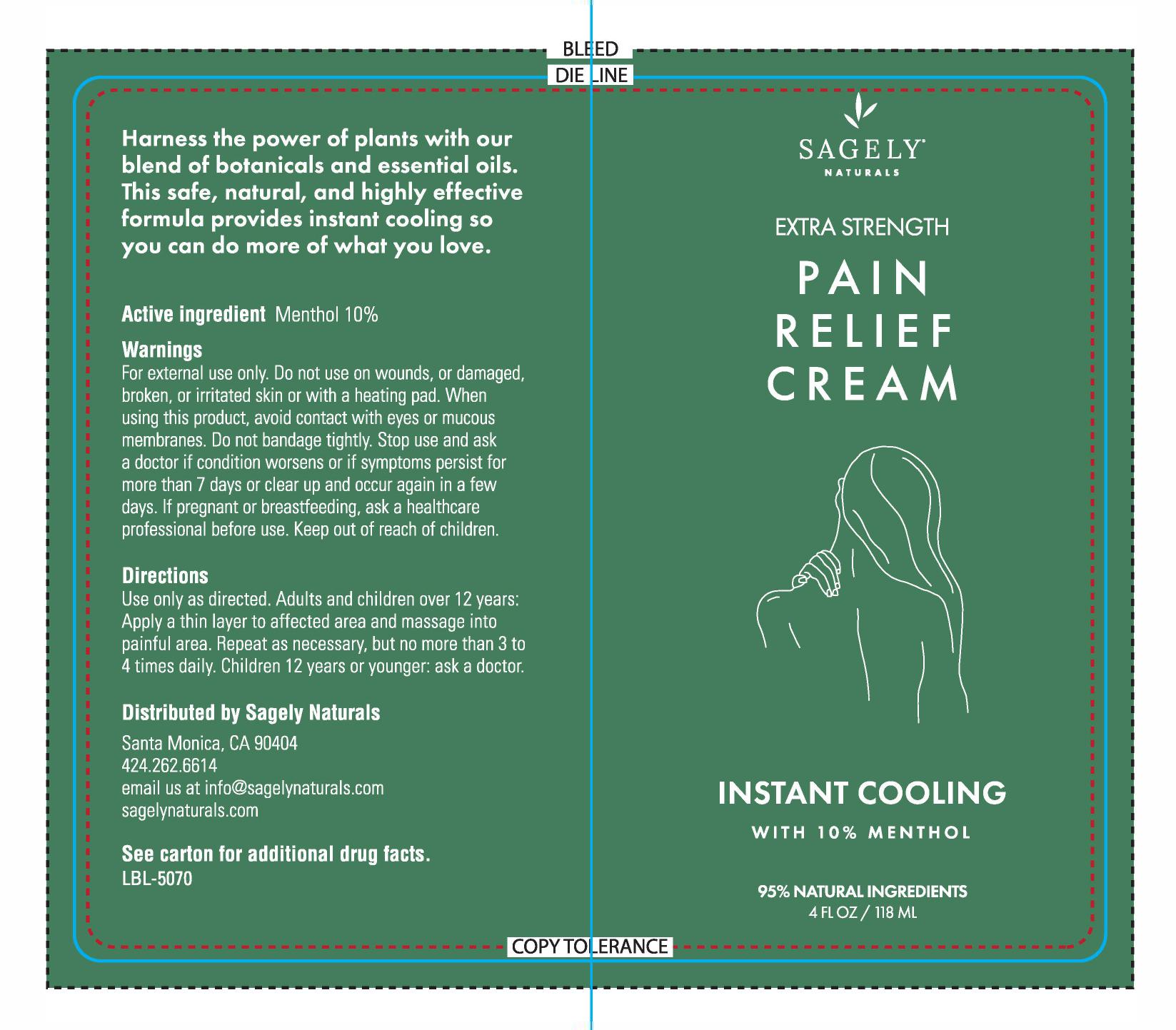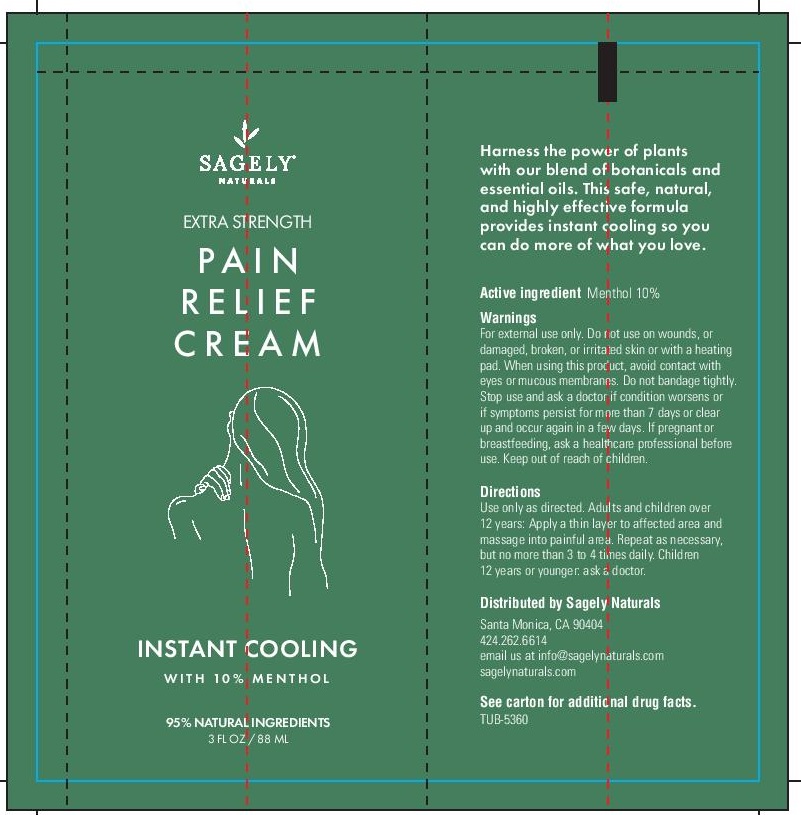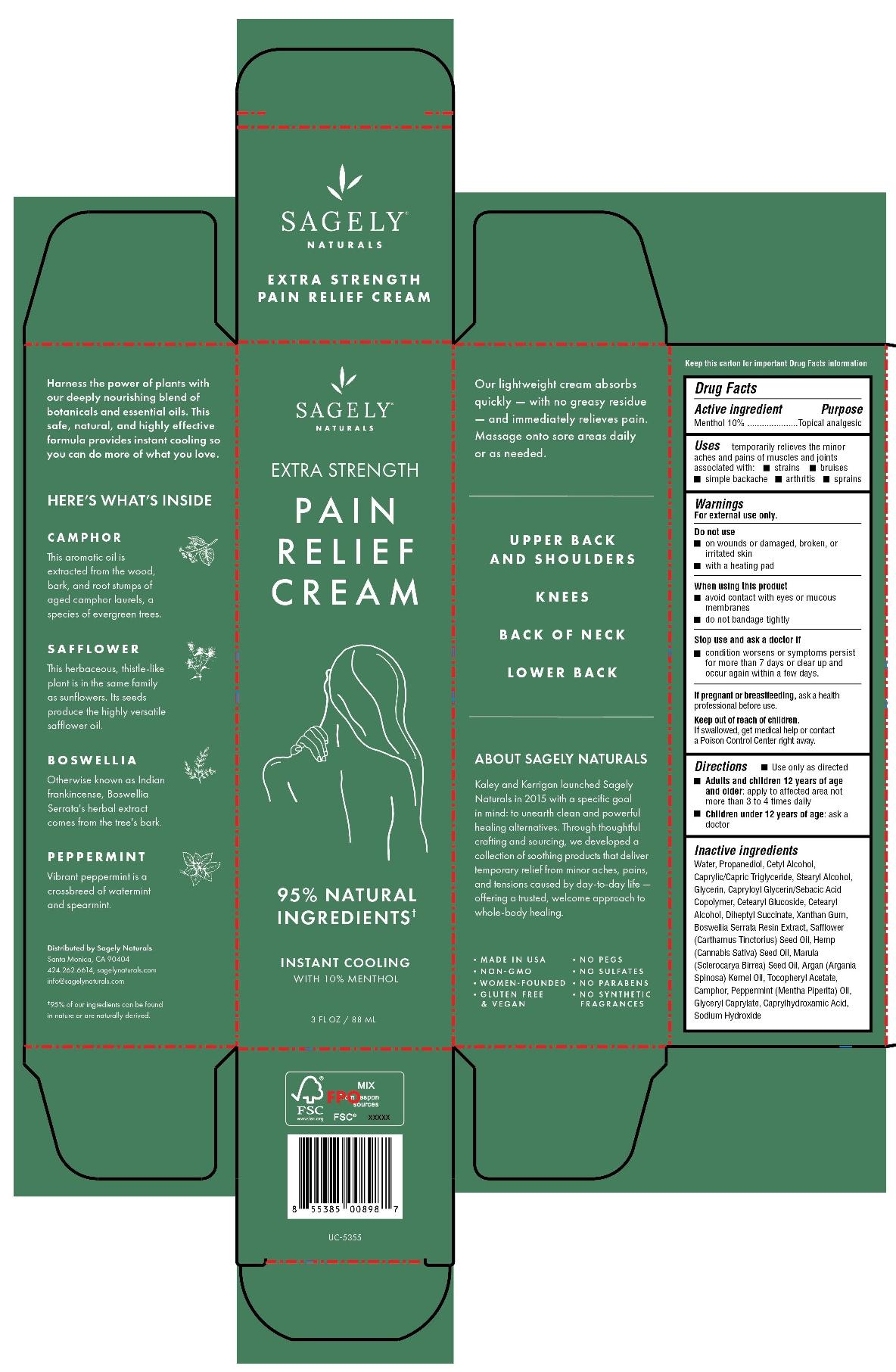 DRUG LABEL: Extra Strength Pain Relief Cream
NDC: 82075-415 | Form: CREAM
Manufacturer: Sagely Enterprises Inc.
Category: otc | Type: HUMAN OTC DRUG LABEL
Date: 20211119

ACTIVE INGREDIENTS: MENTHOL 10 g/100 g
INACTIVE INGREDIENTS: SAFFLOWER OIL; CANNABIS SATIVA SEED OIL; PEPPERMINT OIL; GLYCERYL CAPRYLATE; CAPRYLHYDROXAMIC ACID; PROPANEDIOL; WATER; GLYCERIN; BOSWELLIA SERRATA RESIN OIL; SCLEROCARYA BIRREA SEED OIL; ARGAN OIL; MEDIUM-CHAIN TRIGLYCERIDES; CETYL ALCOHOL; DIHEPTYL SUCCINATE; CAMPHOR (NATURAL); CETOSTEARYL ALCOHOL; STEARYL ALCOHOL; CAPRYLOYL GLYCERIN/SEBACIC ACID COPOLYMER (2000 MPA.S); CETEARYL GLUCOSIDE; .ALPHA.-TOCOPHEROL ACETATE; SODIUM HYDROXIDE; XANTHAN GUM

Extra Strength Pain Relief Cream

Active ingredient

Menthol 10%

Purpose

Menthol 10%..............Topical analgesic

Uses

temporarily relieves the minor aches and pains of muscles and joints associated with:

- strains
- bruises
- simple backache
- arthritis
- sprains

Warnings

For external use only.

Do not use

- on wounds or damaged, broken, or irritated skin
- with a heating pad

When using this product

- avoid contact with eyes or mucous membranes
- do not bandage tightly

Stop use and ask a doctor if

- condition worsens or symptoms persist for more than 7 days or clear up and occur again wtihin a few days.

PREGNANCY OR BREAST FEEDING

If pregnant or breastfeeding, ask a health professional before use.

Keep out of reach of children. If swallowed, get medical help or contact a Poison Control Center right away.

Directions

- Use only as directed
- Adults and children 12 years of age and older: apply to affected area not more than 3 to 4 times daily
- Children under 12 years of age: ask a doctor

Inactive ingredients

Water, Propanediol, Cetyl Alcohol, Caprylic/Capric Triglyceride, Stearyl Alcohol, Glycerin, Capryloyl Glycerin/Sebacic Acid Copolymer, Cetearyl Glucoside, Cetearyl Alcohol, Diheptyl Succinate, Xanthan Gum, Boswellia Serrata Resin Extract, Safflower (Carthamus Tinctorius) Seed Oil, Hemp (Cannabis Sativa) Seed Oil, Marula (Sclerocarya Birrea) Seed Oil, Argan (Argania Spinosa) Kernel Oil, Tocopheryl Acetate, Camphor, Peppermint (Mentha Piperita) Oil, Glyceryl Caprylate, Caprylhydroxamic Acid, Sodium Hydroxide

PACKAGE LABEL

Sagely Naturals

Extra Strength Pain Relief Cream

Instant Cooling

With 10% Menthol

95% Natural Ingredients

4 FL OZ / 118 ML